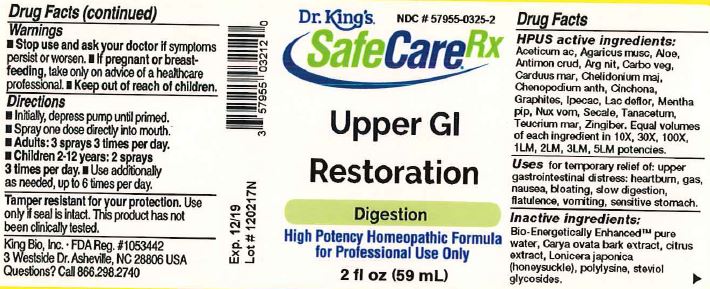 DRUG LABEL: Upper GI Restoration
NDC: 57955-0325 | Form: LIQUID
Manufacturer: King Bio Inc.
Category: homeopathic | Type: HUMAN OTC DRUG LABEL
Date: 20180131

ACTIVE INGREDIENTS: ACETIC ACID 10 [hp_X]/59 mL; AMANITA MUSCARIA FRUITING BODY 10 [hp_X]/59 mL; ALOE 10 [hp_X]/59 mL; ANTIMONY TRISULFIDE 10 [hp_X]/59 mL; SILVER NITRATE 10 [hp_X]/59 mL; ACTIVATED CHARCOAL 10 [hp_X]/59 mL; MILK THISTLE 10 [hp_X]/59 mL; CHELIDONIUM MAJUS 10 [hp_X]/59 mL; DYSPHANIA AMBROSIOIDES 10 [hp_X]/59 mL; CINCHONA OFFICINALIS BARK 10 [hp_X]/59 mL; GRAPHITE 10 [hp_X]/59 mL; IPECAC 10 [hp_X]/59 mL; SKIM MILK 10 [hp_X]/59 mL; MENTHA PIPERITA 10 [hp_X]/59 mL; STRYCHNOS NUX-VOMICA SEED 10 [hp_X]/59 mL; CLAVICEPS PURPUREA SCLEROTIUM 10 [hp_X]/59 mL; TANACETUM VULGARE TOP 10 [hp_X]/59 mL; TEUCRIUM MARUM 10 [hp_X]/59 mL; GINGER 10 [hp_X]/59 mL
INACTIVE INGREDIENTS: WATER; CARYA OVATA BARK; CITRUS BIOFLAVONOIDS; LONICERA JAPONICA FLOWER; POLYEPSILON-LYSINE (4000 MW); REBAUDIOSIDE A

Upper GI Restoration™

HPUS active ingredients:

Aceticum ac, Agaricus musc, Aloe, Antimon crud, Arg nit, Carbo veg, Carduus mar, Chelidonium maj, Chenopodium anth, Cinchona, Graphites, Ipecac, Lac deflor, Mentha pip, Nux vom, Secale, Tanacetum, Teucrium mar, Zingiber.

Equal volumes of each ingredient in 10X, 30X, 100X, 1LM, 2LM, 3LM, 5LM potencies.

INDICATIONS AND USAGE

Uses for temporary relief of: upper gastrointestinal distress: heartburn, gas, nausea, bloating, slow digestion, flatulence, vomiting, sensitive stomach.

Inactive Ingredients:

Bio-Energetically Enhanced™ pure water, Carya ovata bark extract, citrus extract, Lonicer japonica (honeysuckle), polylysine, steviol glycosides

Warnings

- Stop use and ask your doctor if symptoms persist or worsen.
- If pregnant or breast-feeding, take only on advice of a healthcare professional.

- Keep out of reach of children.

Directions

- Initially, depress pump until primed.
- Spray one dose directly into mouth.
- Adults: 3 sprays 3 times per day
- Children 2-12 years: 2 sprays 3 times per day
- Use additionally as needed, up to 6 times per day.

OTHER SAFETY INFORMATION

Tamper resistant for your protection. Use only if safety seal is intact. This product has not been clinically tested.

PURPOSE

Uses for temporary relief of symptoms of upper gastrointestinal distress:

- heartburn
- gas
- nausea
- bloating
- slow digestion
- flatulence
- vomiting
- sensitive stomach